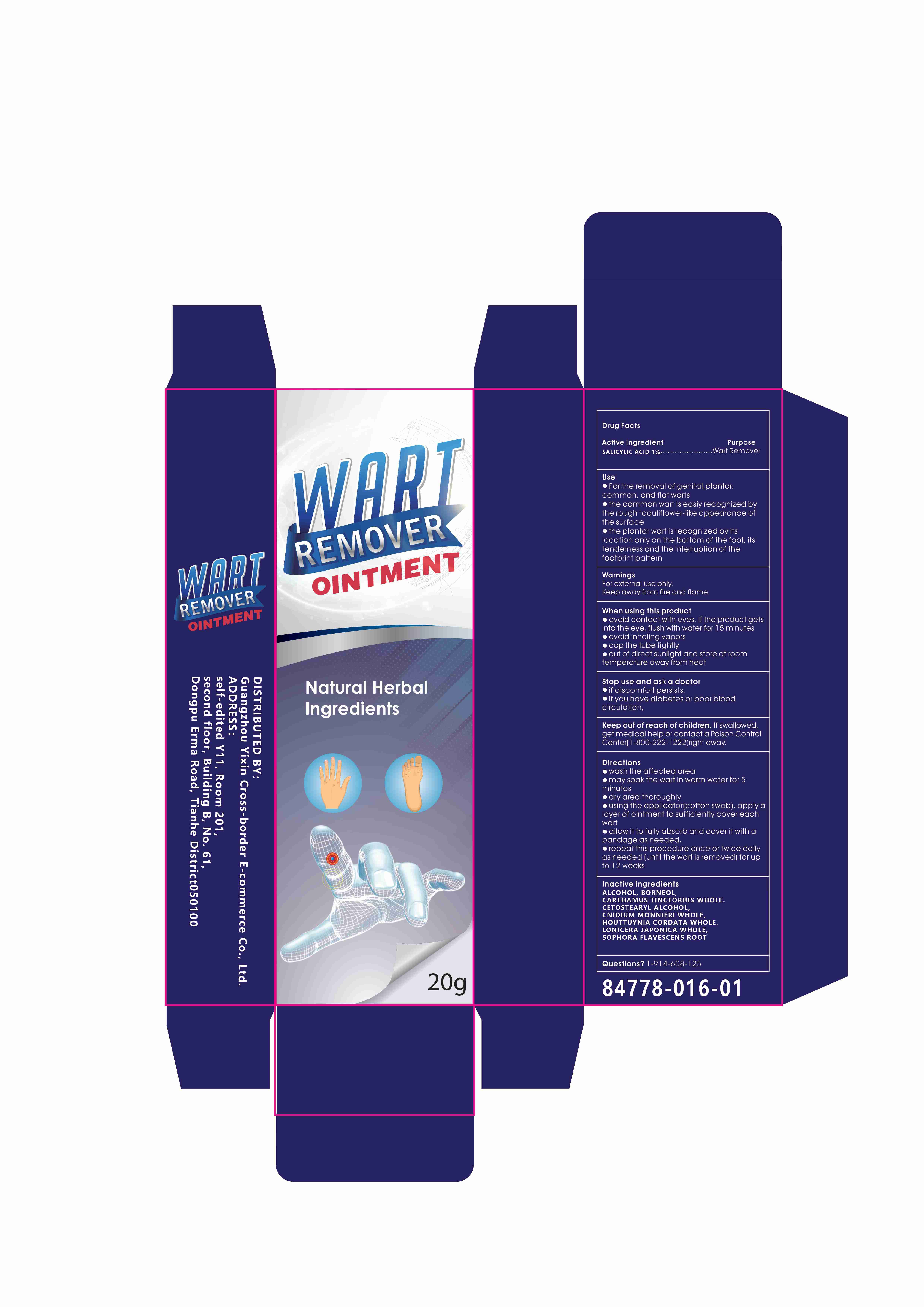 DRUG LABEL: Natural Herbal Ingredients
NDC: 83885-010 | Form: POULTICE
Manufacturer: Guangzhou Guocui Biotechnology Co., Ltd
Category: otc | Type: HUMAN OTC DRUG LABEL
Date: 20241119

ACTIVE INGREDIENTS: SALICYLIC ACID 2 g/20 g
INACTIVE INGREDIENTS: CETOSTEARYL ALCOHOL; CARTHAMUS TINCTORIUS WHOLE; CNIDIUM MONNIERI WHOLE; HOUTTUYNIA CORDATA WHOLE; LONICERA JAPONICA WHOLE; BORNEOL; SOPHORA FLAVESCENS ROOT; ALCOHOL

Active ingredients

SALICYLIC ACID 1%....Wart Remover

Purpose

For the removal of genital,plantar

common, and flat warts

the common wart is easiyrecognized by

the rough "cauliflower-like appearance of

the surface

the plantar wart is recognized by its

location only on the bottom of the foot, its

tenderness and the interruption of the

footprint pattern

Uses

For the removal of genital,plantar

common, and flat warts

the common wart is easiyrecognized by

the rough "cauliflower-like appearance of

the surface

the plantar wart is recognized by its

location only on the bottom of the foot, its

tenderness and the interruption of the

footprint pattern

Warnings

For external use only.

Keep away from fire and flame

Dosage and administration

For external use only.

Do not use

Stop use and ask a doctor if

chest pain, rapid heartbeat, faintness, or dizziness occurs

sudden, unexplained weight gain occurs

your hands or feet swell

scalp irritation or redness occurs

unwanted facial hair growth occurs

you do not see hair regrowth in 4 months

May be harmful if used when pregnant or breast-feeding.

Keep out of reach of children, lf swallowed, get medical help or contact a Poison Control Center right away.

When using section

wash the affected ared

omay soak the wart in warm water for 5

minutes

edry area thoroughly

using the applicator(cotton swab), apply a

layer of ointment to sufficiently cover each

wart

allow it to fully absorb and cover it with a

bandage as needed

erepeat this procedure once or twice daily

as needed (until the wart is removed) for up

to 12 weeks

stop use

on broken or irritated scalp

Keep out of reach of children. lf swallowed

get medical help or contact a Poison Control

Center(1-800-222-1222)right away

Inactive ingredients

ALCOHOL, BORNEOL, CARTHAMUS TINCTORIUS WHOLE.

CETOSTEARYL ALCOHOL, CNIDIUM MONNIERI WHOLE,

HOUTTUYNIA CORDATA WHOLE,LONICERA JAPONICA WHOLE,SOPHORA FLAVESCENS ROOT